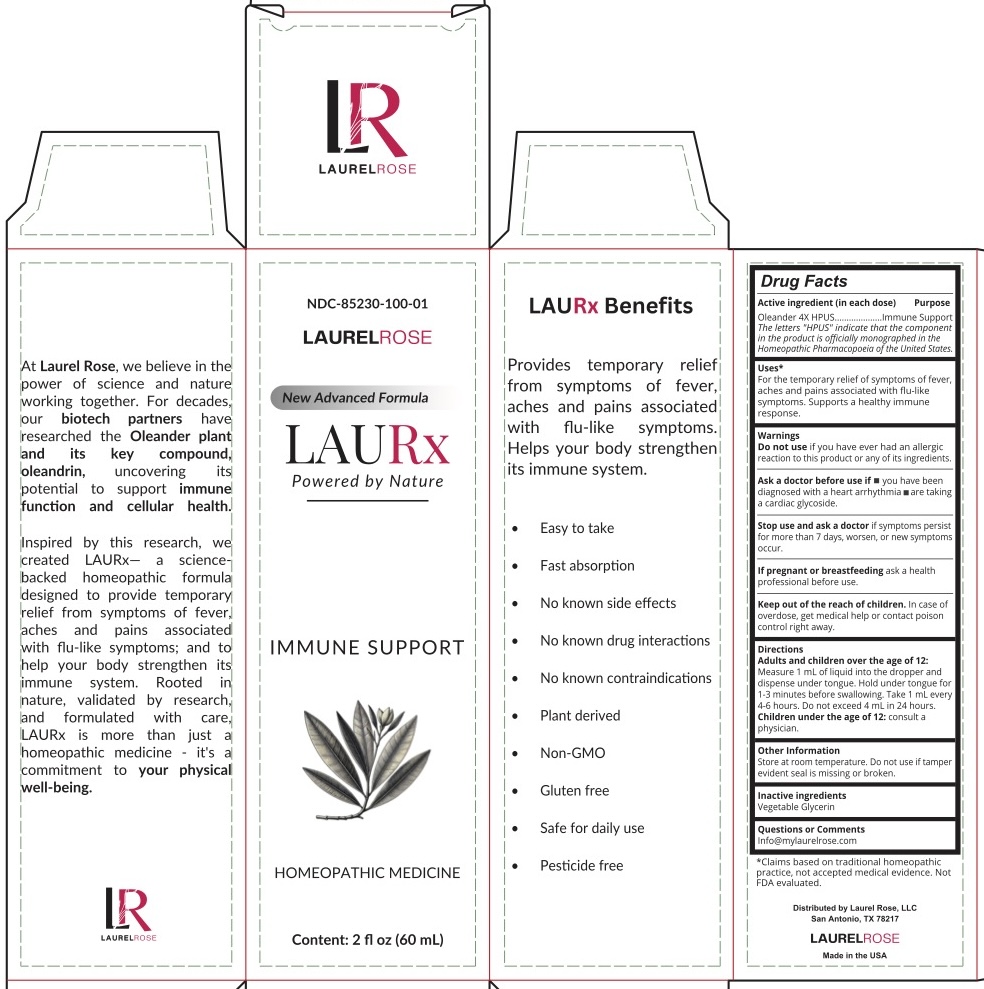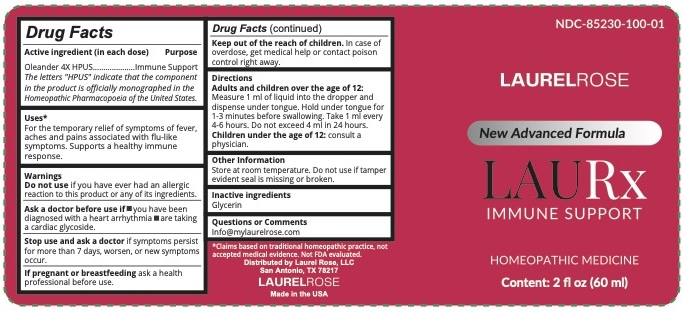 DRUG LABEL: LAURx IMMUNE SUPPORT
NDC: 85230-100 | Form: LIQUID
Manufacturer: Laurel Rose LLC
Category: homeopathic | Type: HUMAN OTC DRUG LABEL
Date: 20251110

ACTIVE INGREDIENTS: NERIUM OLEANDER LEAF 4 [hp_X]/30 mL
INACTIVE INGREDIENTS: GLYCERIN

LAURx IMMUNE SUPPORT

Active Ingredient (in each 1ml dose)

Oleander HPUS* 4X

The letters "HPUS" indicate that the component in the product is officially monographed in the Homeopathic Phormacopoeia of the United States.

Purpose

Immune Support

Inactive Ingredients

Glycerin

Uses

For the temporary relief of symptoms of fever, associated with flu-like symptoms. Supports a healthy immune response.

Warning

if you have ever had an allergic reaction to this product or any of its ingredients.

If pregnant or breastfeeding ask a health professional before use.

Keep out of the reach of children. In case of overdose, get medical help or contact poison control right away.

Stop use and ask a doctor if symptoms persist for more than 7 days, worsen, or new symptoms occur

Ask doctor

Ask a doctor before use if you have been diagnosed with a heart arrhythmia are taking a cardiac glycoside.

Directions

Adults and children over the age of 12:

Measure 1 ml of liquid into the dropper and dispense under tongue. Hold under tongue for

1-3 minutes before swallowing. Take 1 ml every

4-6 hours. Do not exceed 4 ml in 24 hours.

Children under the age of 12: consult a physician.

Other Information

Store at room temperature. Do not use if tamper evident seal is missing or broken.

Questions or Comments

Info@mylaurelrose.com